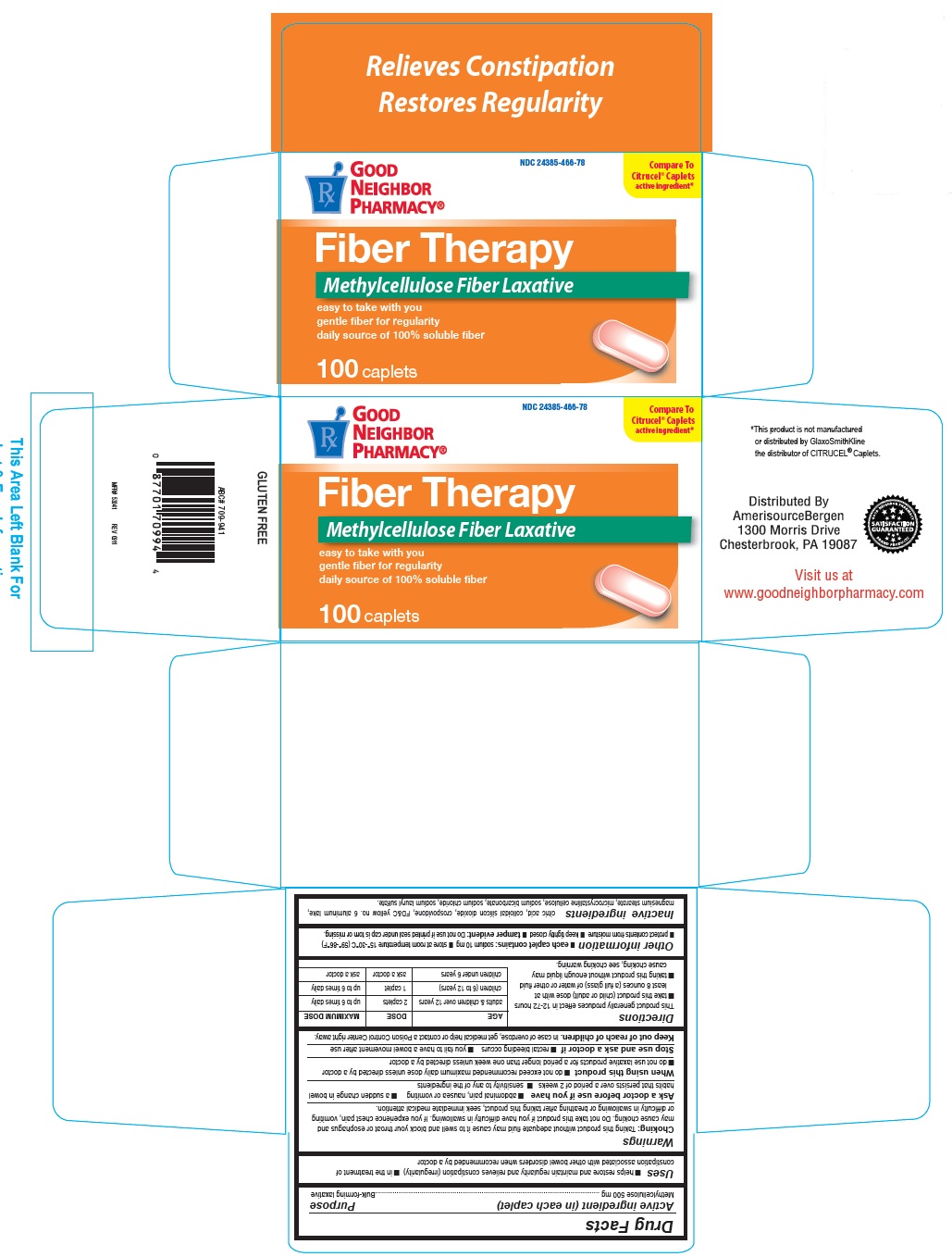 DRUG LABEL: GNP Fiber Therapy
NDC: 24385-466 | Form: TABLET
Manufacturer: Amerisource Bergen
Category: otc | Type: HUMAN OTC DRUG LABEL
Date: 20250120

ACTIVE INGREDIENTS: METHYLCELLULOSE (4000 CPS) 500 mg/1 1
INACTIVE INGREDIENTS: ANHYDROUS CITRIC ACID; SILICON DIOXIDE; CROSPOVIDONE; FD&C YELLOW NO. 6; MAGNESIUM STEARATE; SODIUM BICARBONATE; SODIUM CHLORIDE; SODIUM LAURYL SULFATE

GNP Fiber Therapy Caplets

Active ingredient (in each caplet)

Methylcellulose 500 mg

Purpose

Bulk-forming laxative

Uses

- helps restore and maintain regularity and relieves constipation (irregularity)
- in the treatment of constipation associated with other bowel disorders when recommended by a doctor

Warnings

Choking: Taking this product without adequate fluid may cause it to swell and block your throat or esophagus and may cause choking. Do not take this product if you have difficulty in swallowing. If you experience chest pain, vomiting or difficulty in swallowing or breathing after taking this product, seek immediate medical attention.

Ask a doctor before use if you have

- abdominal pain, nausea or vomiting
- a sudden change in bowel habits that persists over a period of 2 weeks
- sensitivity to any of the ingredients

When using this product

- do not exceed recommended maximum dose unless directed by a doctor
- do not use laxative products for a period longer than one week unless directed by a doctor

Stop use and ask a doctor if

- rectal bleeding occurs
- you fail to have a bowel movement after use

Keep out of reach of children

In case of overdose, get medical help or contact a poison control center right away.

Directions

This product generally produces effect in 12-72 hours

take this product (child or adult) dose with atleast 8 ounces (a full glass) of water or other fluid

taking this product without enough liquid may cause choking, see choking warning

AGE | DOSE | MAXIMUM DOSE
adults and children over 12 years | 2 caplets | up to 6 times daily
children (6 to 12 years) | 1 caplet | up to 6 times daily
children under 6 years | ask a doctor | ask a doctor

Other information

- each caplet contains: sodium 10 mg
- store at room temperature 15o-30oC (59o-86oF)
- protect contents from moisture
- keep tightly closed
- tamper evident: Do not use if printed seal under cap is torn or missing

Inactive ingredients

citric acid, colloidal silicon dioxide, crospovidone, FD&C yellow 6 aluminum lake, magnesium stearate, microcrystalline cellulose, sodium bicarbonate, sodium chloride, sodium lauryl sulphate

Principal Display Panel

Good Neighbor Pharmacy

compare to Citrucel caplets active ingredient

fiber therapy

Methylcellulose Fiber Laxativebulk-forming laxative

easy to take with you

gentle fiber for regularity

daily source of 100% soluble fiber

100 caplets